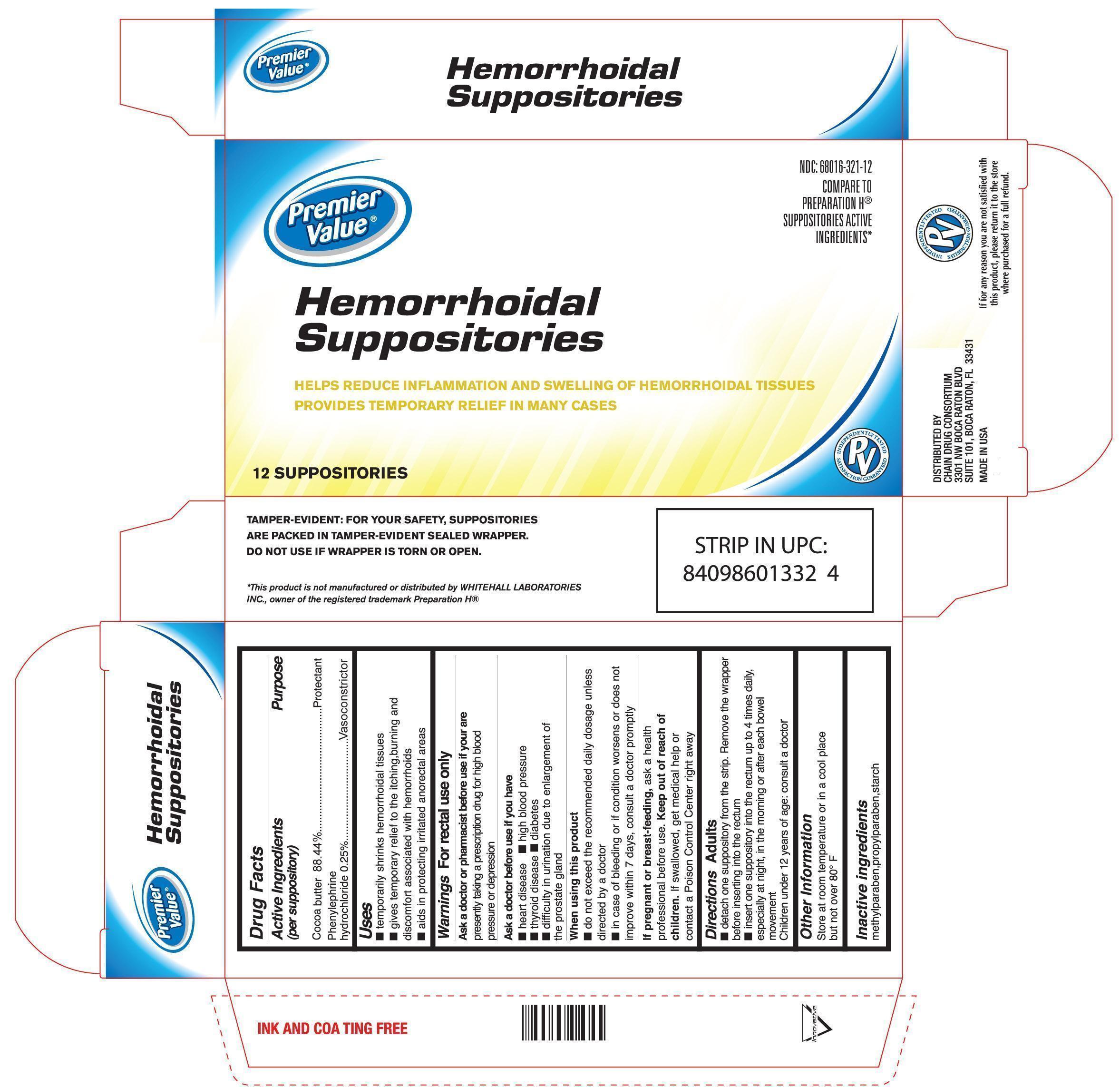 DRUG LABEL: Premier Value Hemorrhoidal
NDC: 68016-321 | Form: SUPPOSITORY
Manufacturer: Chain Drug Consortium
Category: otc | Type: HUMAN OTC DRUG LABEL
Date: 20150325

ACTIVE INGREDIENTS: COCOA BUTTER 88.44 g/100 g; PHENYLEPHRINE HYDROCHLORIDE .25 g/100 g
INACTIVE INGREDIENTS: METHYLPARABEN .02 g/100 g; PROPYLPARABEN .02 g/100 g; MODIFIED CORN STARCH (1-OCTENYL SUCCINIC ANHYDRIDE) 11.27 g/100 g

Drug Facts

Active Ingredients Purpose

(per suppository)

Cocoa butter 88.44%...................................................................Protectant

Phenylephrine hydrochloride 0.25%..............................................Vasoconstrictor

Uses

- temporarily shrinks hemorrhoidal tissues
- gives temporary relief to the itching, burning, and discomfort associated with hemorrhoids
- aids in protecting irritated anorectal areas

Warnings

For rectal use only

Directions

Adults

- detach one suppository from the strip. Remove the wrapper before inserting into the rectum
- insert one suppository into the rectum up to 4 times daily, especially at night, in the morning or after each bowel movement

Children under 12 years of age: consult a doctor

Other information

Store at room temperature or in a cool place but not over 80oF

Inactive ingredients

methylparaben, propylparaben, starch

Ask a doctor or pharmacist before use if you are presently taking a prescription drug for high blood pressure or depression

Ask a doctor before use if you have

-heart disease -high blood pressure

-thyroid disease -diabetes
-difficulty in urination due to enlargement of the prostate gland

When using this product

-do not exceed the recommended daily dosage unless directed by a doctor
-in case of bleeding or if condition worsens or does not improve within 7 days, consult a doctor promptly

If pregnant or breast-feeding, ask a health professional before use.

Keep out of reach of children. If swallowed, get medical help or contact a Poison Control Center right away